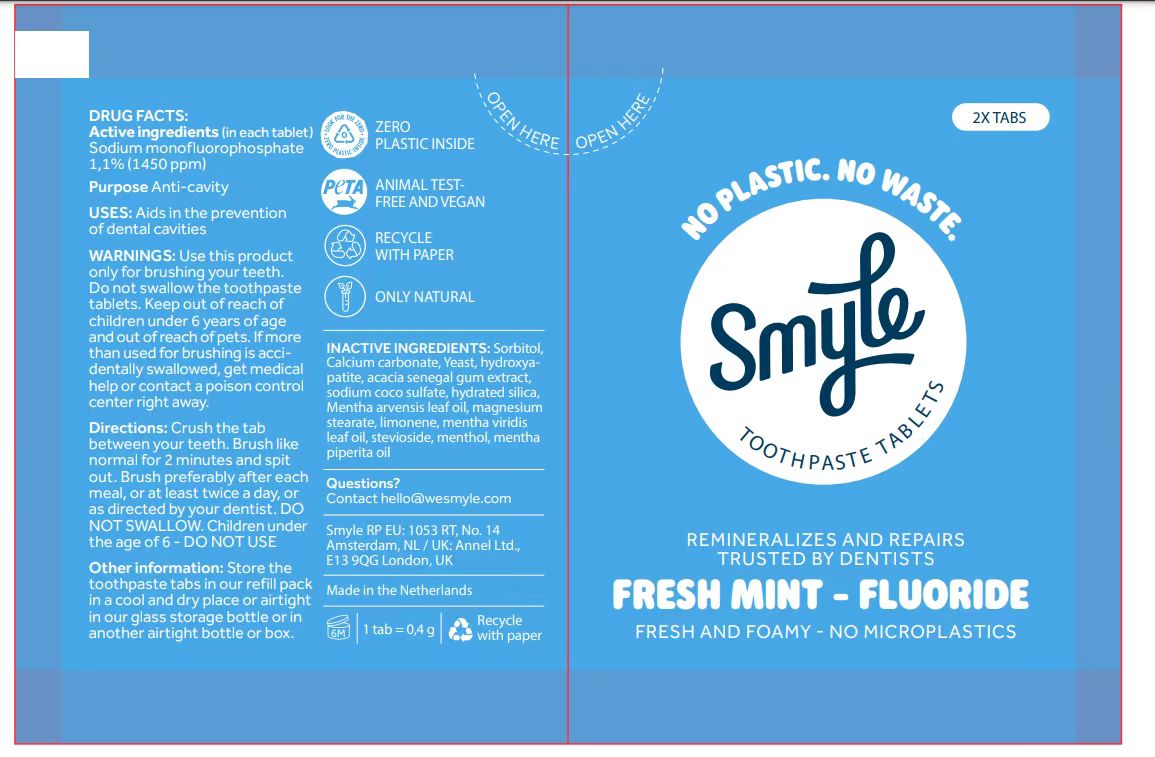 DRUG LABEL: Tooth
NDC: 83861-005 | Form: TABLET
Manufacturer: Henan Dailygreen Biotechnology Co. LTD
Category: otc | Type: HUMAN OTC DRUG LABEL
Date: 20241231

ACTIVE INGREDIENTS: SODIUM MONOFLUOROPHOSPHATE 1.1 g/100 1
INACTIVE INGREDIENTS: CALCIUM CARBONATE; MENTHA ARVENSIS LEAF OIL; MAGNESIUM STEARATE; SODIUM COCO-SULFATE; YEAST; ACACIA SENEGAL GUM; MENTHOL; STEVIOSIDE; MENTHA VIRIDIS (SPEARMINT) LEAF OIL; MENTHA PIPERITA (PEPPERMINT) OIL; HYDRATED SILICA; SORBITOL; LIMONENE, (+)-; HYDROXYAPATITE

83861-005

Active ingredient

Sodium monofluorophosphate 1,1%(1450ppm)

Purpose

Anti-cavity

Use

Aids in the prevention of dental cavities

Warnings

Use this product only for brushing your teeth.Do not swallow the toothpaste tabiets. Keep out of reach of children under 6 years of age and out of reach of pets. If more than used for brushing is accidentally swallowed, get medical help or contact a poison control center right away.

Do not swallow the toothpaste tabiets.

WHEN USING

n/a

STOP USE

n/a

Keep out of reach of children under 6 years of age and out of reach of pets.

Directions

Crush the tab between your teeth. Brush like normal for 2 minutes and spit out.Brush preferably after each meal, or at least twice a day, or as directed by your dentist. DO NOT SWALLOW.Children under the age of6 - DO NOT USE

Other Information

Store the toothpaste tabs in our refill pack in a cool and dry place or airtight in our glass storage bottle or in another airtight bottle or box.

Inactive ingredients

Sorbitol,Calcium carbonate, Yeast, hydroxyapatite, acacia senegal gum extract, sodium coco sulfate, hydrated silica, Mentha arvensis leaf oil, magnesium stearate, limonene, mentha viridis leaf oil, stevioside, menthol, mentha piperita oil